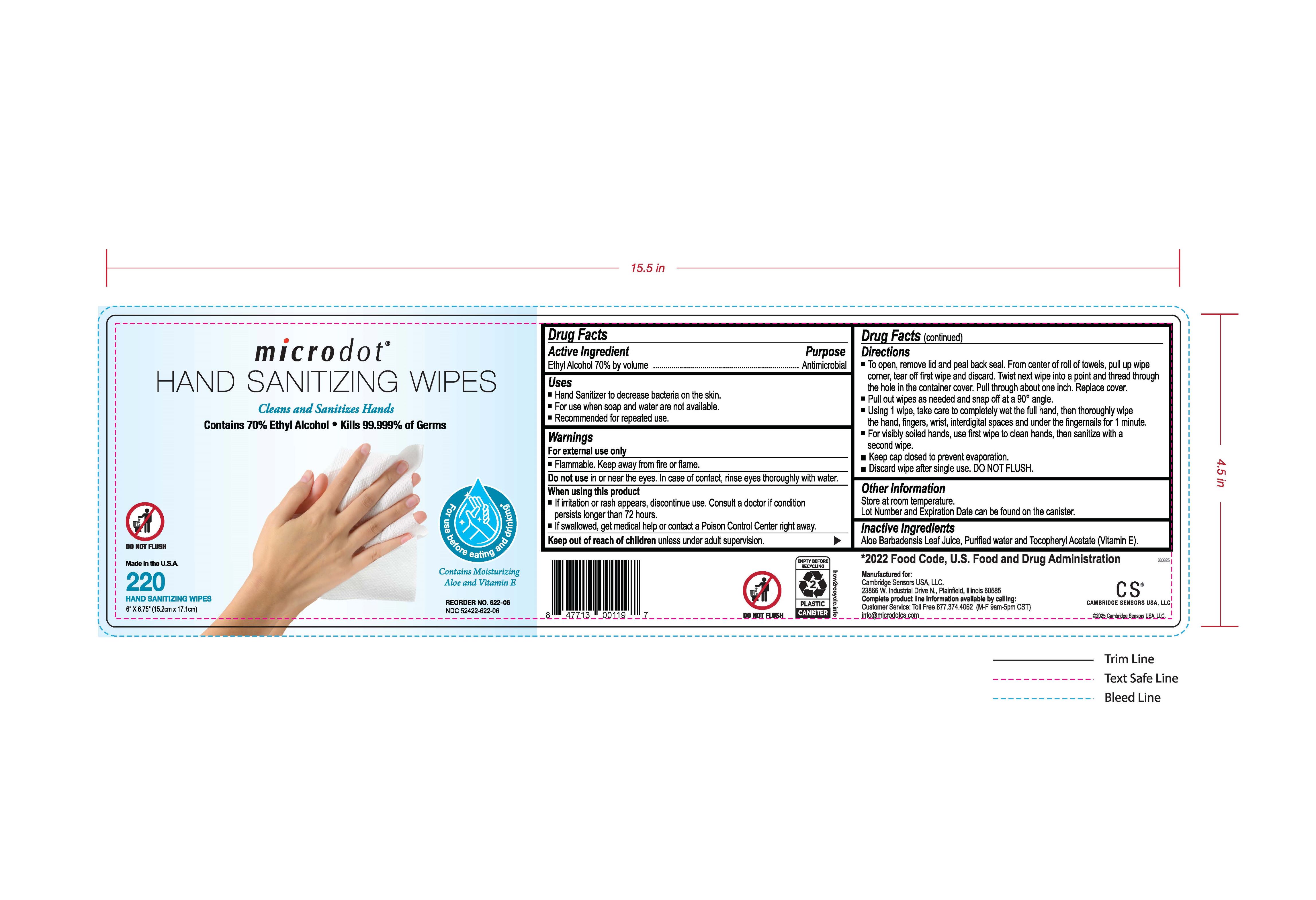 DRUG LABEL: microdot Hand Sanitizing Wipe
NDC: 52422-622 | Form: LIQUID
Manufacturer: Cambridge Sensors USA, LLC
Category: otc | Type: HUMAN OTC DRUG LABEL
Date: 20250624

ACTIVE INGREDIENTS: ALCOHOL 70 mL/100 mL
INACTIVE INGREDIENTS: WATER

microdot Hand Sanitizing Wipe

PURPOSE

Antiseptic Hand Sanitizing Wipe

ACTIVE INGREDIENT

Ethyl Alcohol 70.0 (w / w)

INDICATIONS AND USAGE

Hand sanitizer to decrease bacteria on the skin.
For use when soap and water are not available.
Recommended for repeated use.

WARNINGS

For external use only
Flammable. Keep away from fire or flame.

Do not use in or near the eyes. In case of contact, rinse eyes thoroughly with water.

WHEN USING

If irritation or rash appears, discontinue use. Consult a doctor if a condition persists longer than 72 hours.
If swallowed, get medical help or contact a Poision Control Center right away.

Keep out of reach of children unless under adult supervision.

DOSAGE AND ADMINISTRATION

To open, remove lid and peal back seal. From center of roll of towels, pull up wipe corner, tear off first wipe and discard. Twist next wipe into a point and trhead through the hole in the container cover. Pull through about one inch. Replace cover.
Pull out wipes as needed and snap off at a 90° angle.

Using 1 wipe, take care to completely wet the full hand, then thoroughly wipe the hand, fingers, wrist, interdigital spaces and under the fingernails for 1 minute.
For visibly soiled hands, use first wipe to clean hands, then sanitize with a second wipe.

Keep cap closed to prevent evaporation.
Discard wipe after single use. DO NOT FLUSH.

OTHER SAFETY INFORMATION

Store at room temperature.

Lot Number and Expiration date can be found on the canister.

INACTIVE INGREDIENT

Aloe Barbadensis Leaf Juice, Purified water and Tocopheryl Acetate (Vitamin E).

Product Label Image.